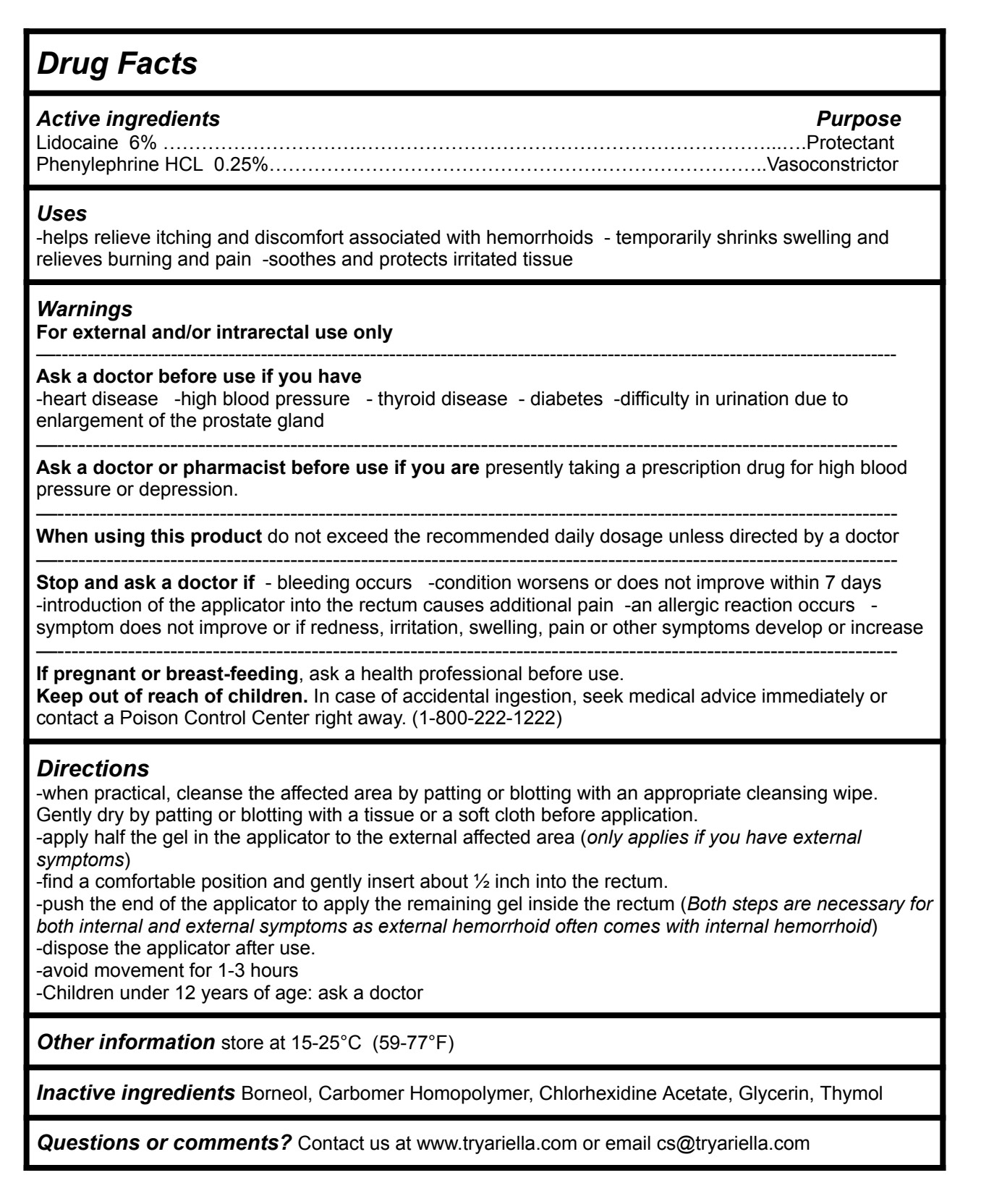 DRUG LABEL: Ariella Hemorrhoid Gel
NDC: 83364-022 | Form: OINTMENT
Manufacturer: YITONGBADA (SHENZHEN) INTERNATIONAL TRADE CO., LTD
Category: otc | Type: HUMAN OTC DRUG LABEL
Date: 20250924

ACTIVE INGREDIENTS: PHENYLEPHRINE HYDROCHLORIDE 0.25 g/100 g; LIDOCAINE 4 g/100 g
INACTIVE INGREDIENTS: BORNEOL; CARBOMER HOMOPOLYMER, UNSPECIFIED TYPE; GLYCERIN; CHLORHEXIDINE ACETATE; THYMOL

Ariella Hemorrhoid Gel

Drug Facts

Active ingredients Purpose

Lidocaine 6% ………………………….………...….Protectant Phenylephrine HCL 0.25%…………………………………………….……………………..Vasoconstrictor

DOSAGE AND ADMINISTRATION

For external and/or intrarectal use only

Ask a doctor before use if you have

-heart disease -high blood pressure - thyroid disease - diabetes -difficulty in urination due to enlargement of the prostate gland

Ask a doctor or pharmacist before use if you are presently taking a prescription drug for high blood pressure or depression.

When using this product do not exceed the recommended daily dosage unless directed by a doctor

ASK DOCTOR

Stop and ask a doctor if - bleeding occurs -condition worsens or does not improve within 7 days -introduction of the applicator into the rectum causes additional pain -an allergic reaction occurs - symptom does not improve or if redness, irritation, swelling, pain or other symptoms develop or increase

PREGNANCY OR BREAST FEEDING

If pregnant or breast-feeding, ask a health professional before use.

Keep out of reach of children. In case of accidental ingestion, seek medical advice immediately or contact a Poison Control Center right away. (1-800-222-1222)

Uses

-helps relieve itching and discomfort associated with hemorrhoids - temporarily shrinks swelling and relieves burning and pain -soothes and protects irritated tissue

Warnings

Directions

-when practical, cleanse the affected area by patting or blotting with an appropriate cleansing wipe. Gently dry by patting or blotting with a tissue or a soft cloth before application.

-apply half the gel in the applicator to the external affected area (only applies if you have external symptoms)

-find a comfortable position and gently insert about ½ inch into the rectum.

-push the end of the applicator to apply the remaining gel inside the rectum (Both steps are necessary for both internal and external symptoms as external hemorrhoid often comes with internal hemorrhoid)

-dispose the applicator after use.

-avoid movement for 1-3 hours

-Children under 12 years of age: ask a doctor

Other information store at 15-25°C (59-77°F)

Inactive ingredients

Borneol, Carbomer Homopolymer, Chlorhexidine Acetate, Glycerin, Thymol